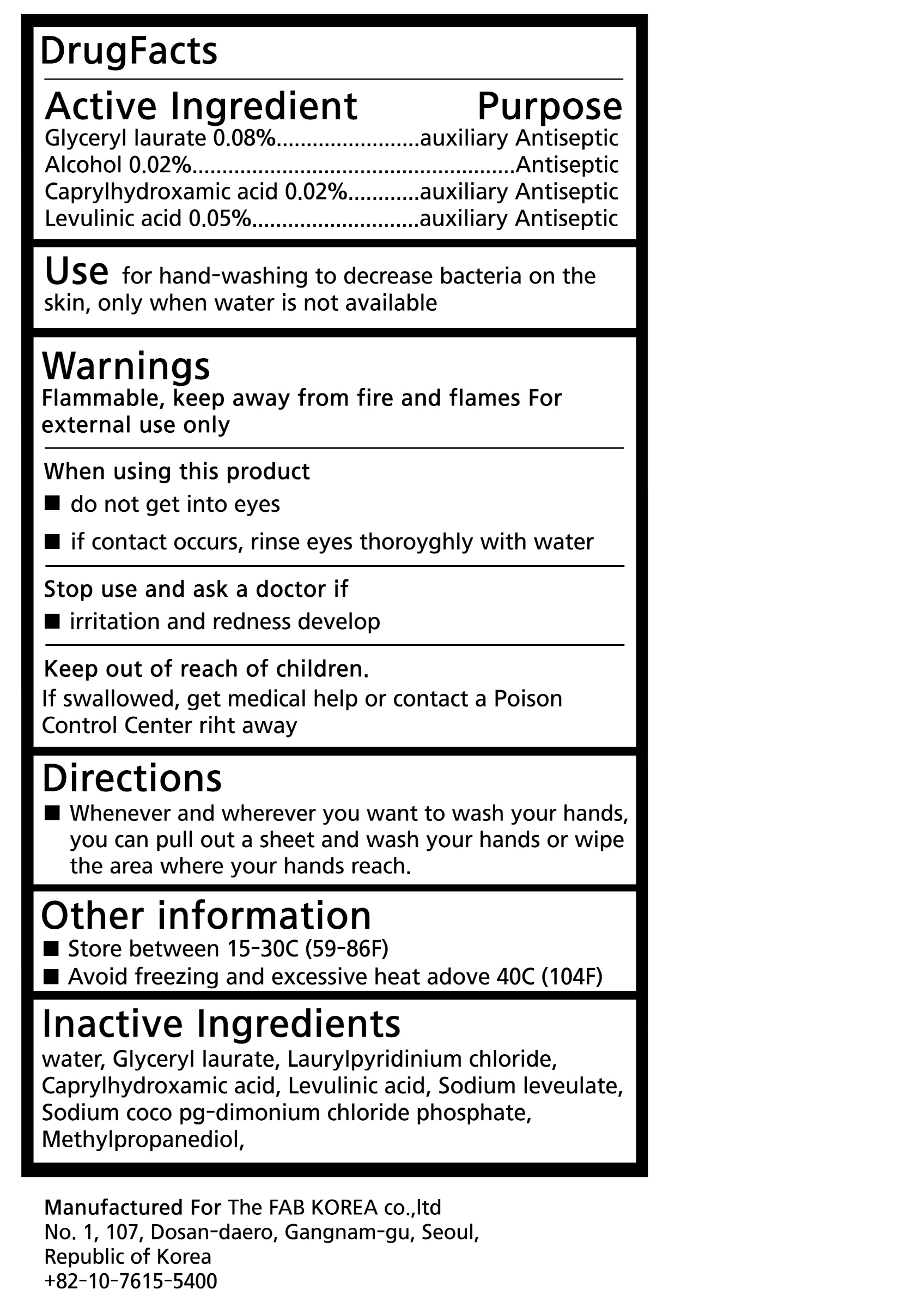 DRUG LABEL: Purus antibacterial wipes
NDC: 77504-0004 | Form: CLOTH
Manufacturer: The fab Korea Co., Ltd.
Category: otc | Type: HUMAN OTC DRUG LABEL
Date: 20200902

ACTIVE INGREDIENTS: GLYCERYL LAURATE 0.0448 g/56 g; LEVULINIC ACID 0.028 g/56 g; CAPRYLHYDROXAMIC ACID 0.0112 g/56 g; ALCOHOL 0.0112 mL/56 g
INACTIVE INGREDIENTS: WATER

The fab Korea Co., Ltd. - Purus antibacterial wipes

ACTIVE INGREDIENT

glyceryl laurate, laurylpyridinium chloride, caprylhydroxamic acid, alcohol, levulinic acid

INACTIVE INGREDIENT

sodium coco pg-dimonium chloride phosphate, sodiu levulinate, methyl propanediol, water

PURPOSE

Hand sanitizer to help reduce bacteria that potentially can cause disease. For use when soap and water are not available.

keep out of reach of the children

INDICATIONS AND USAGE

Place enough product on hands to cover all surfaces. Rub hands together until dry.

Supervise children under 6 years of age when using this product to avoid swallowing.

Do not use

- in children less than 2 months of age
- on open skin wounds

When using this product keep out of eyes, ears, and mouth. In case of contact with eyes, rinse thoroughly with water.

Stop use and ask a doctor if irritation or rash occurs. These may be signs of a serious condition.

Keep out of reach of children. If swallowed, get medical help or contact a Poison Control Center right away.

DOSAGE AND ADMINISTRATION

for external use only